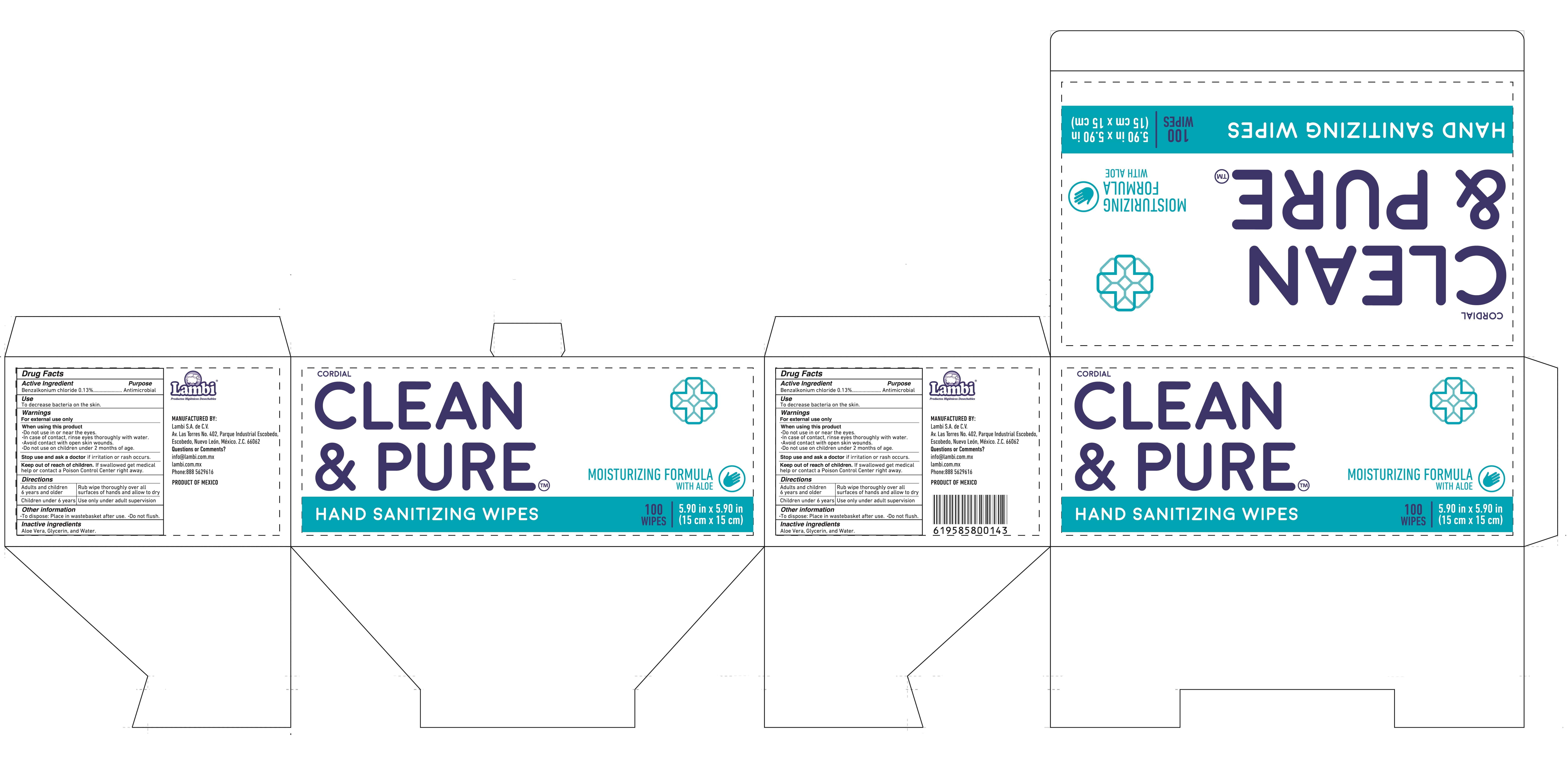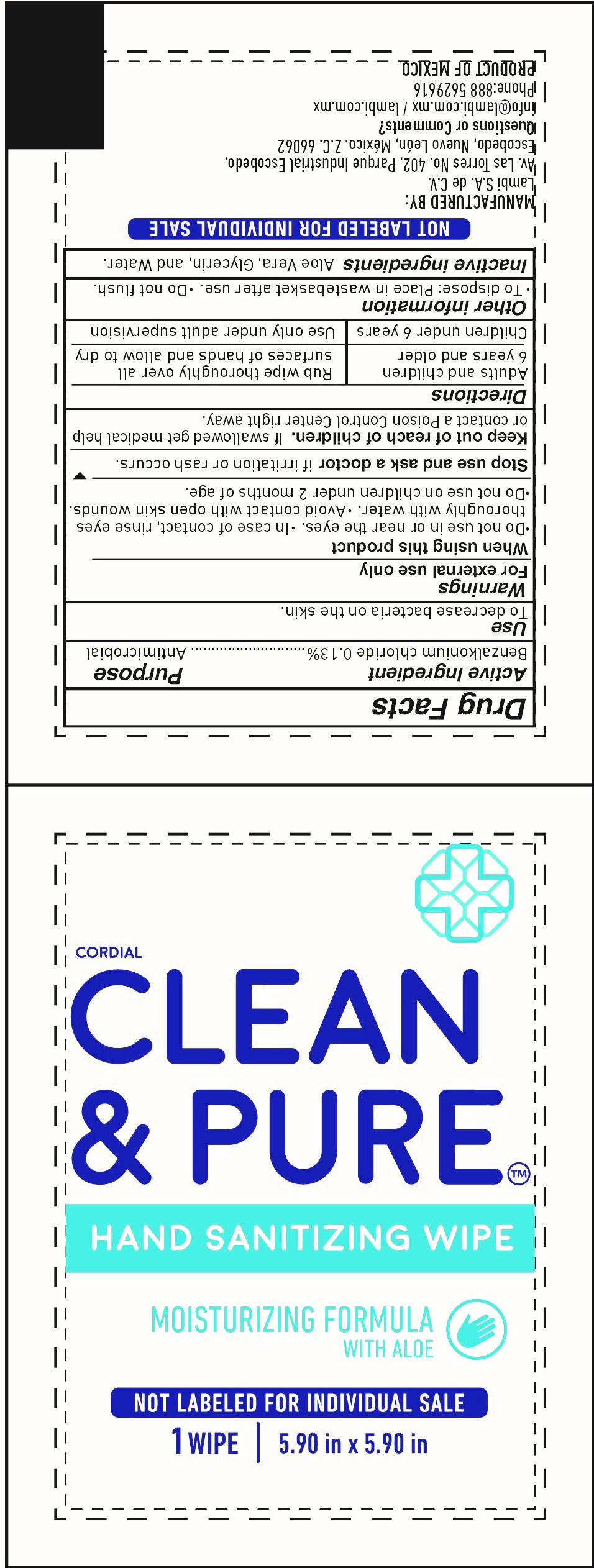 DRUG LABEL: Cordial Clean and Pure
NDC: 81510-001 | Form: CLOTH
Manufacturer: Lambi, S.A. de C.V.
Category: otc | Type: HUMAN OTC DRUG LABEL
Date: 20210528

ACTIVE INGREDIENTS: BENZALKONIUM CHLORIDE 0.13 g/100 g
INACTIVE INGREDIENTS: GLYCERIN; ALOE VERA LEAF; WATER

Hand Sanitizer Wipes

BENZALKONIUM CHLORIDE WIPES

BENZALKONIUM CHLORIDE 0.13% Purpose: Antimicrobial

Purpose

Antimicrobial

Use

To decrease bacteria on the skin

Warnings

For external use only.

When using this product

- Do not use in or near the eyes
- In case of contact rinse eyes thoroughly with water
- Avoid contact with open skin wounds
- Do not use on children under 2 months of age

Stop use and ask a doctor

If irritation or rash occurs.

Keep out of reach of children

If swallowed, get medical help or contact a Poison Control Center right away.

Directions

- Adults and children 6 years and older - Rub wipe thoroughly over all surfaces of hands and allow to dry.
- Children under 6 years - Use only under adult supervision

Other information

- To dispose - Place in waste basket after use
- Do not flush

Inactive ingredients

Aloe Vera, Glycerin and Water

Package Label - Sachet wipe

Sachet wipe NDC 81510-001-02

LAMBI_BOX_100